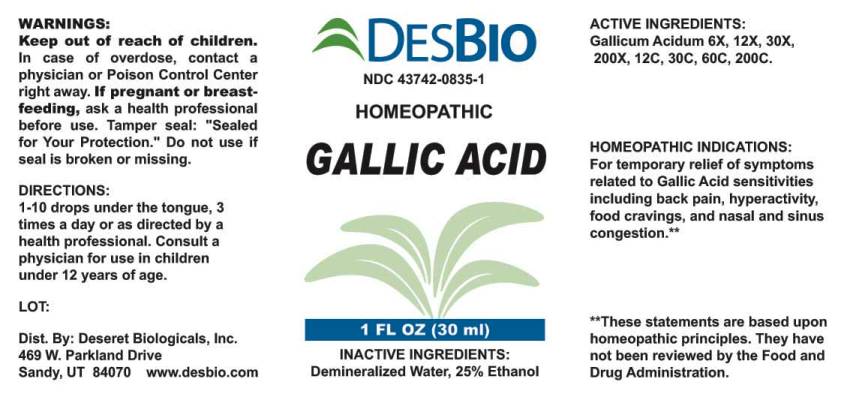 DRUG LABEL: Gallic Acid
NDC: 43742-0835 | Form: LIQUID
Manufacturer: Deseret Biologicals, Inc.
Category: homeopathic | Type: HUMAN OTC DRUG LABEL
Date: 20231213

ACTIVE INGREDIENTS: GALLIC ACID 6 [hp_X]/1 mL
INACTIVE INGREDIENTS: WATER; ALCOHOL

Drug Facts:

ACTIVE INGREDIENT:

Gallicum Acidum 6X, 12X, 30X, 200X, 12C, 30C, 60C, 200C.

HOMEOPATHIC INDICATIONS:

For temporary relief of symptoms related to Gallic Acid sensitivities including back pain, hyperactivity, food cravings, and nasal and sinus congestion.

**These statements are based upon traditional homeopathic principles. They have not been reviewed by the Food and Drug Administration.

WARNINGS:

Keep out of reach of children. In case of overdose, contact physician or a Poison Control Center right away.

If pregnant or breast-feeding, ask a health professional before use.

Tamper seal: "Sealed for Your Protection." Do not use if seal is broken or missing.

Keep out of reach of children. In case of overdose, contact physician or a Poison Control Center right away.

DIRECTIONS:

1-10 drops under the tongue, 3 times a day or as directed by a health professional. Consult a physician for use in children under 12 years of age.

HOMEOPATHIC INDICATIONS:

For temporary relief of symptoms related to Gallic Acid sensitivities including back pain, hyperactivity, food cravings, and nasal and sinus congestion.

**These statements are based upon traditional homeopathic principles. They have not been reviewed by the Food and Drug Administration.

INACTIVE INGREDIENTS:

Demineralized Water, 25% Ethanol

QUESTIONS:

Dist. By: Deseret Biologicals, Inc.

469 W. Parkland Drive

Sandy, UT 84070 www.desbio.com

PACKAGE LABEL DISPLAY:

DESBIO

NDC 43742-0835-1

HOMEOPATHIC

GALLIC ACID

1 FL OZ (30 ml)